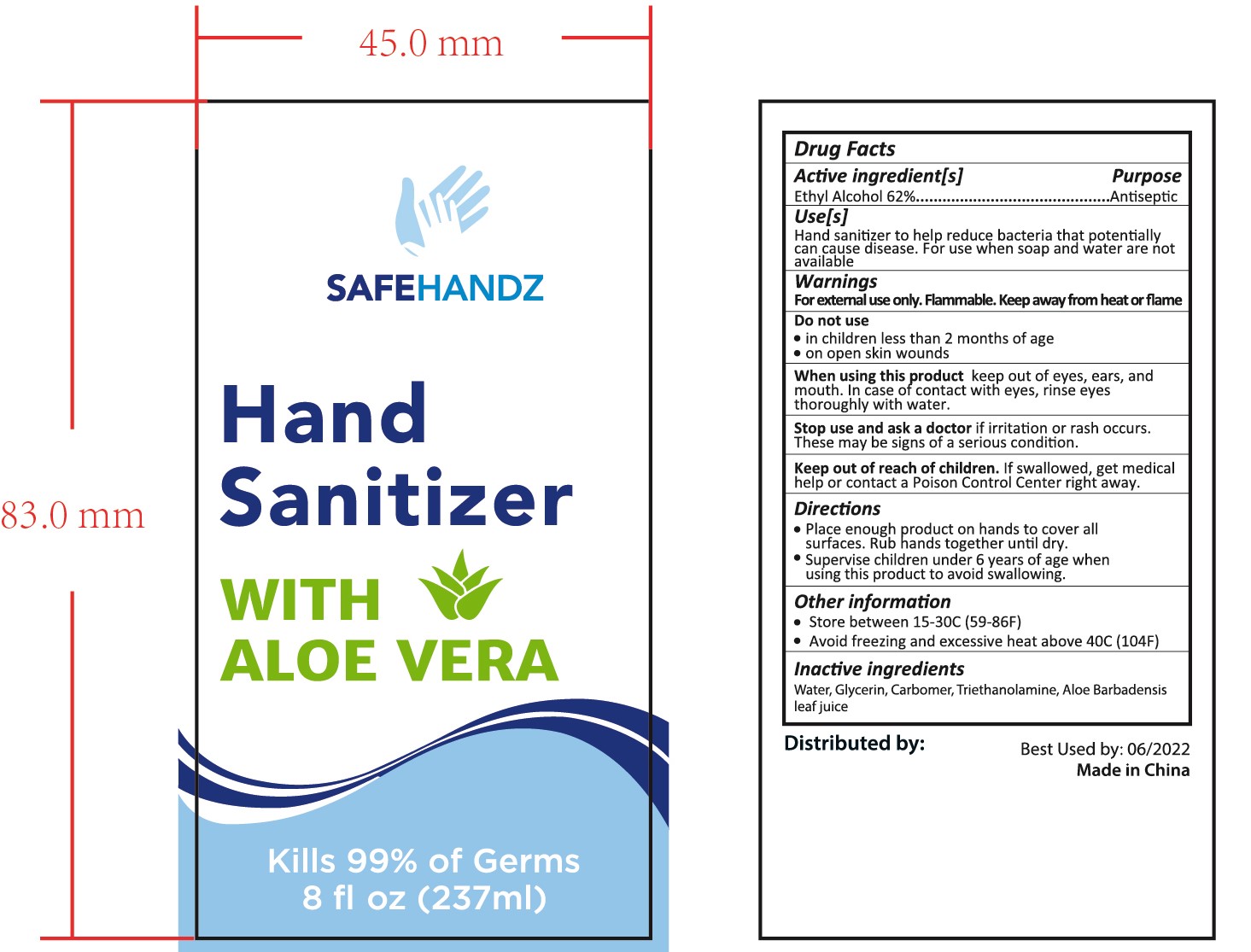 DRUG LABEL: HAND SANITIZER
NDC: 47993-275 | Form: GEL
Manufacturer: NINGBO JIANGBEI OCEAN STAR TRADING CO.,LTD
Category: otc | Type: HUMAN OTC DRUG LABEL
Date: 20201105

ACTIVE INGREDIENTS: ALCOHOL 62 g/112 mL
INACTIVE INGREDIENTS: ALOE VERA LEAF; WATER; GLYCERIN; CARBOMER 940; TRIETHANOLAMINE BENZOATE

47993-275

Active ingredients

Ethyl Alcohol 62%

PURPOSE

Antiseptic

Uses：

Hand sanitizer to help reduce bacteria that potentially can cause disease. For use when soap and water are not available.

Warnings:

For external use only. Flammable，Keep away from heat or flame.

Do not use

in children less than 2 months of age

- on open skin wounds

When using this product keep out of eyes，ears，and mouth. In case of contact with eyes，rinse eyes thoroughly with water.

Stop use and ask a doctor if irritation or rash occurs. These may be signs of a serious condition.

Keep out of reach of children. If swallowed，get medical help or contact a Poison Control Center right away.

Directions:

- Place enough product on hands to cover all surfaces. Rub hands together until dry.
- Supervise children under 6 years of age when using this product to avoid swallowing.

Other information

- Store between 15-30℃（59-86℉）
- Avoid freezing and excessive heat above 40℃（104℉）

Inactive Ingredients:

Water,Glycerin,Carbomer,Triethanolamine,Aloe Barbadensis leaf juice.